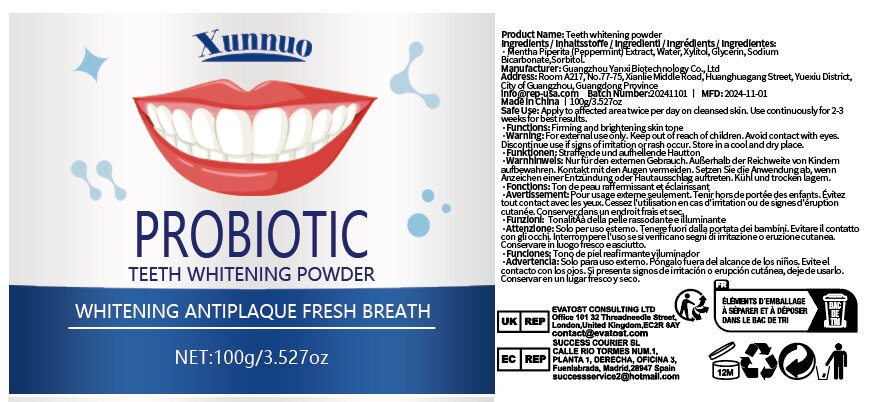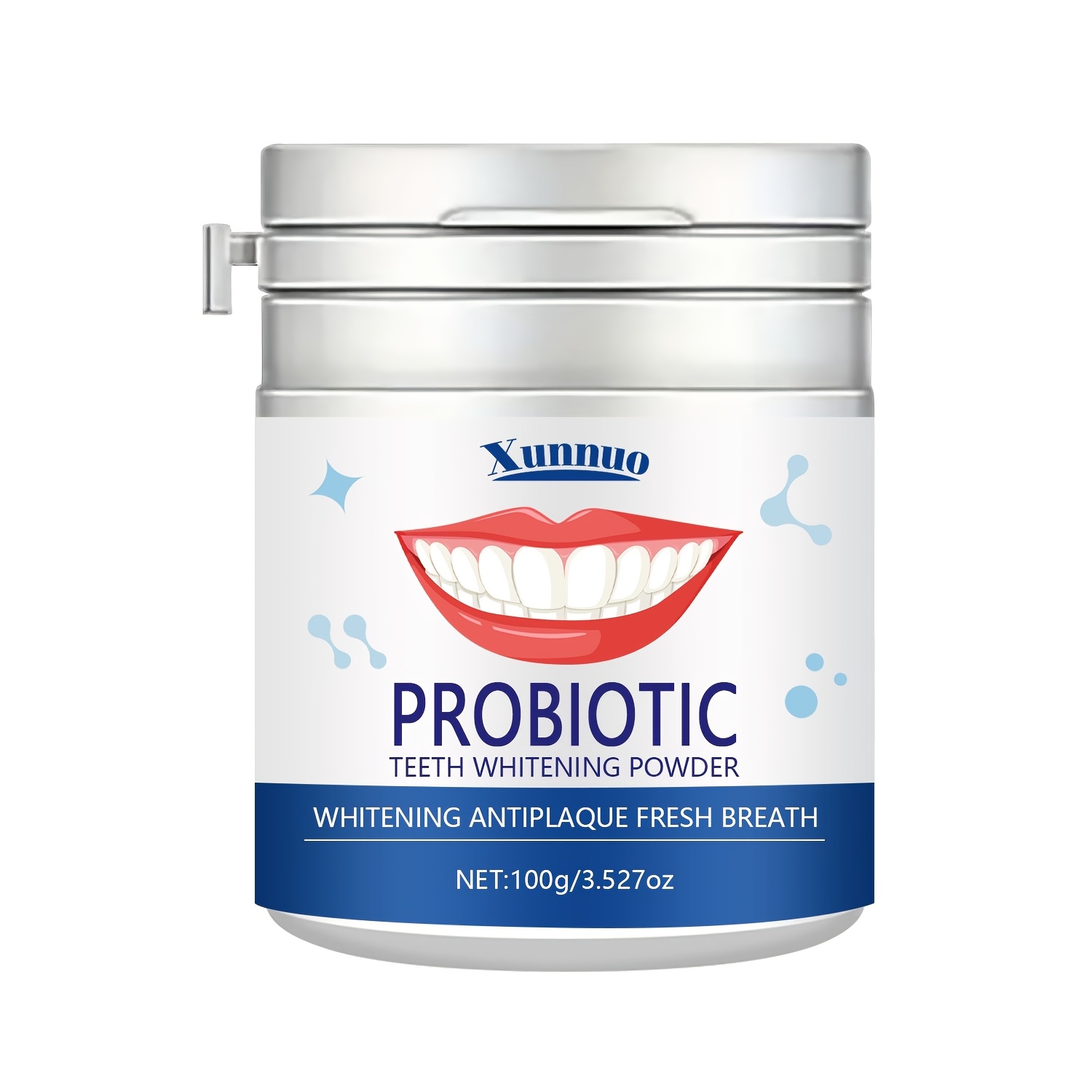 DRUG LABEL: Teeth whitening powder
NDC: 84025-281 | Form: POWDER
Manufacturer: Guangzhou Yanxi Biotechnology Co., Ltd
Category: otc | Type: HUMAN OTC DRUG LABEL
Date: 20241217

ACTIVE INGREDIENTS: GLYCERIN 3 mg/100 g; XYLITOL 5 mg/100 g
INACTIVE INGREDIENTS: WATER

DOSAGE AND ADMINISTRATION

Apply to affected are a twice per day cleansed skin. Use continuously for 2-3 weeks for best results.

WARNINGS

keep out of children

INACTIVE INGREDIENT

Aqua

INDICATIONS AND USAGE

for daily tooth care

Keep out of children

PURPOSE

Teeth cleaning and whitening